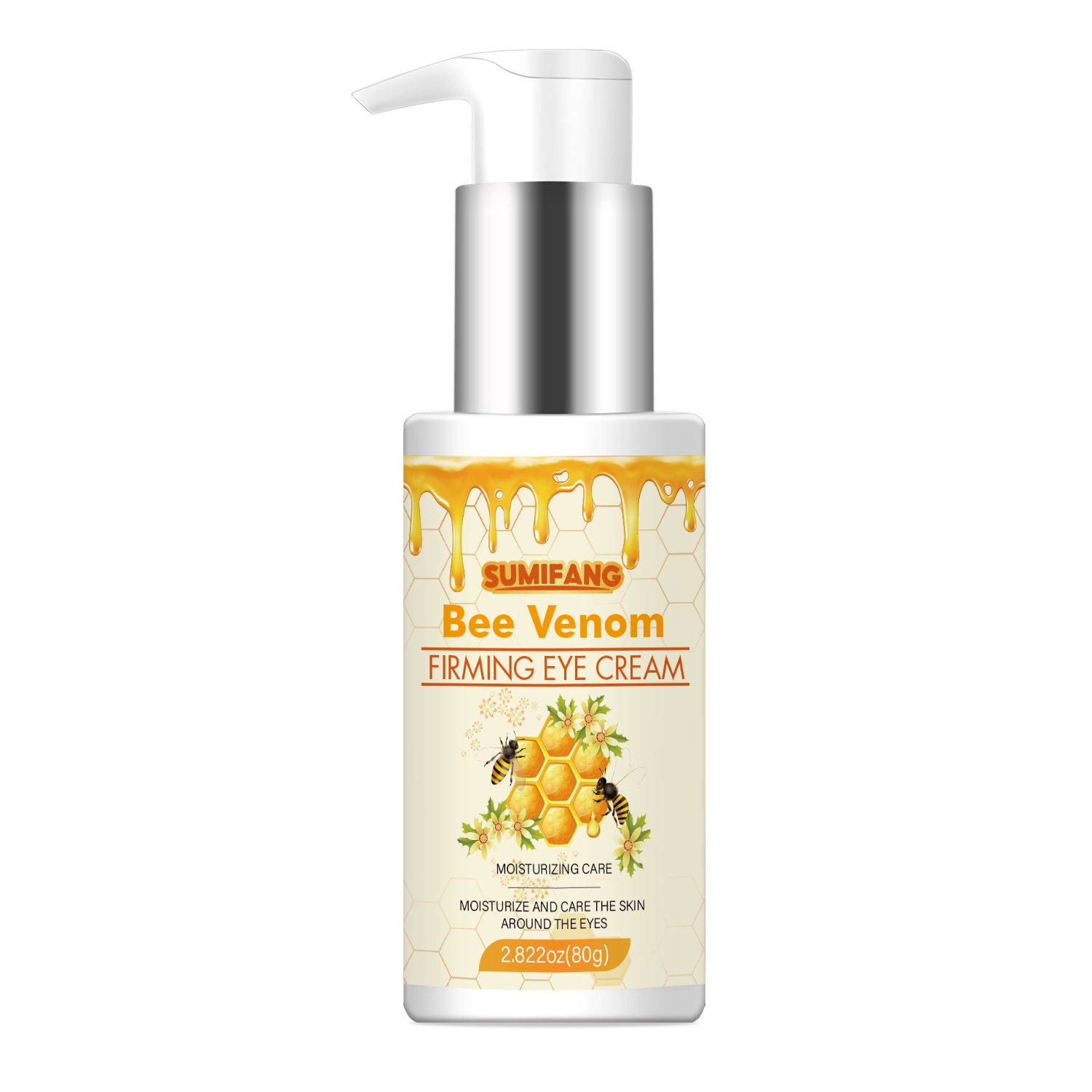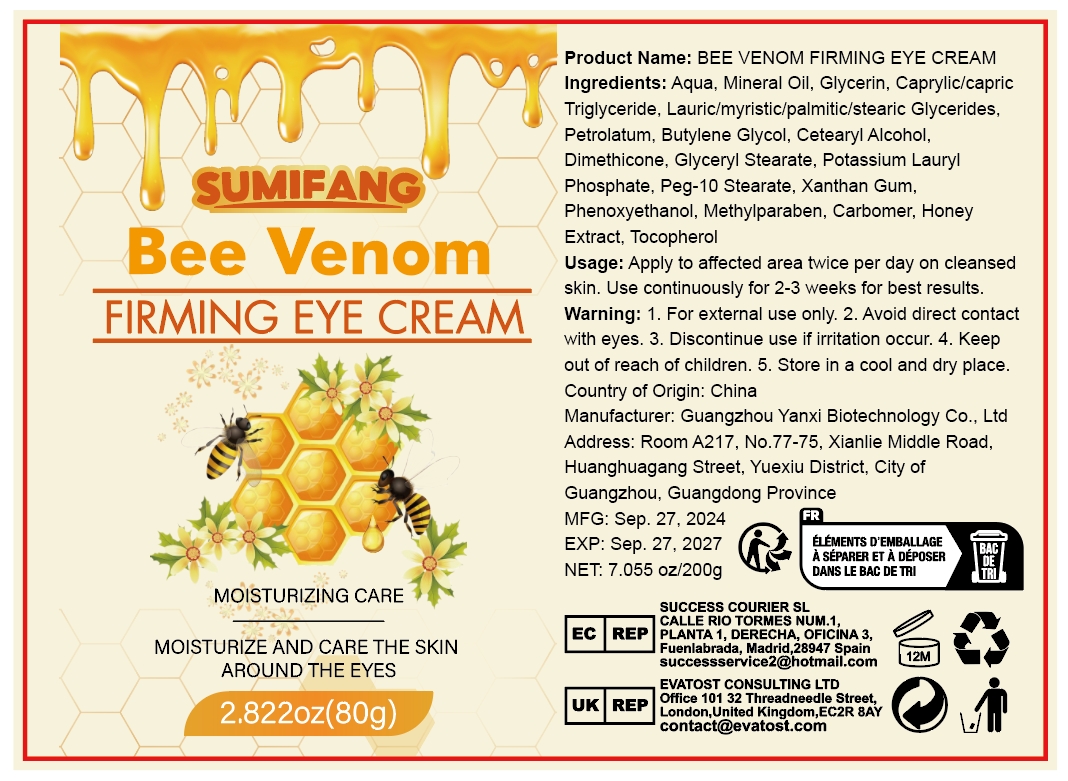 DRUG LABEL: Eye Firming Cream
NDC: 84025-200 | Form: CREAM
Manufacturer: Guangzhou Yanxi Biotechnology Co., Ltd
Category: otc | Type: HUMAN OTC DRUG LABEL
Date: 20241008

ACTIVE INGREDIENTS: NIACINAMIDE 5 mg/100 mL; CETEARYL OLIVATE 3 mg/100 mL
INACTIVE INGREDIENTS: WATER

DOSAGE AND ADMINISTRATION

use as normal eye cream

WARNINGS

Keep out of children

INACTIVE INGREDIENT

Aqua

INDICATIONS AND USAGE

for eye care

keep out of children

PURPOSE

Moisturize and moisturize the eye area